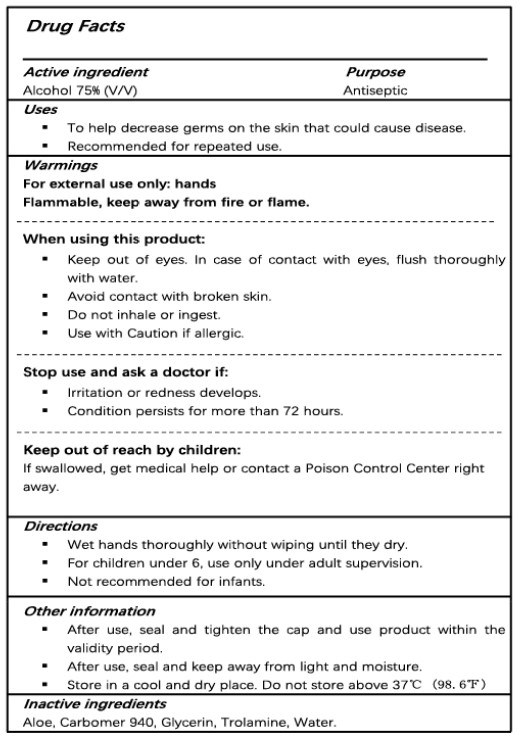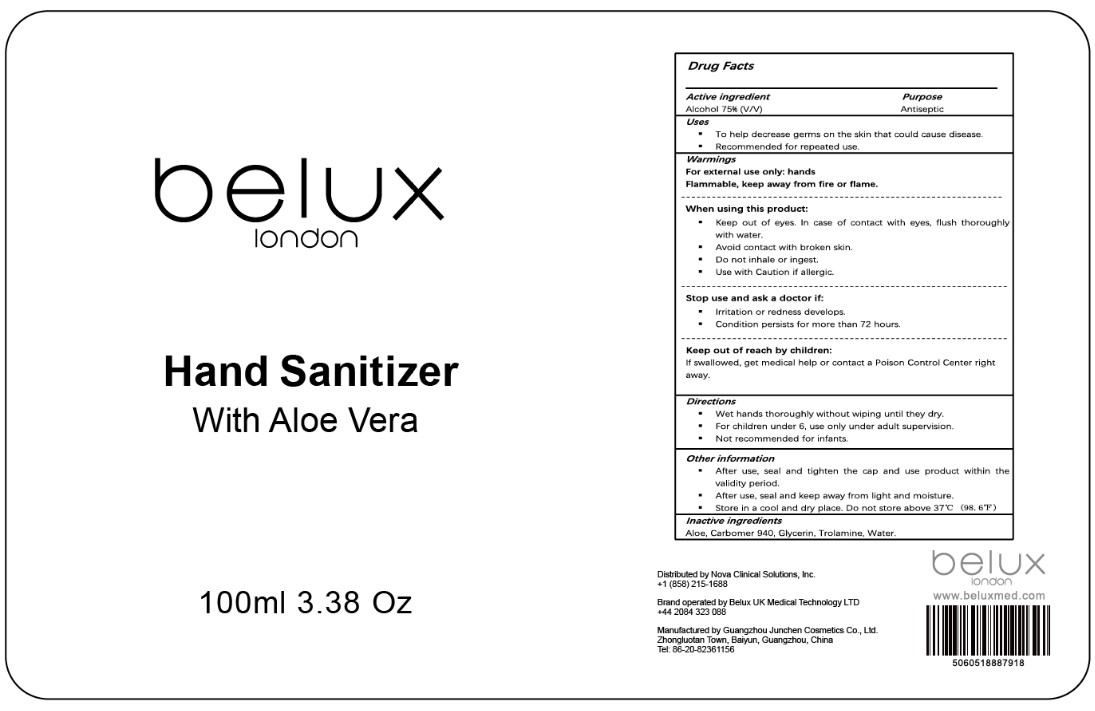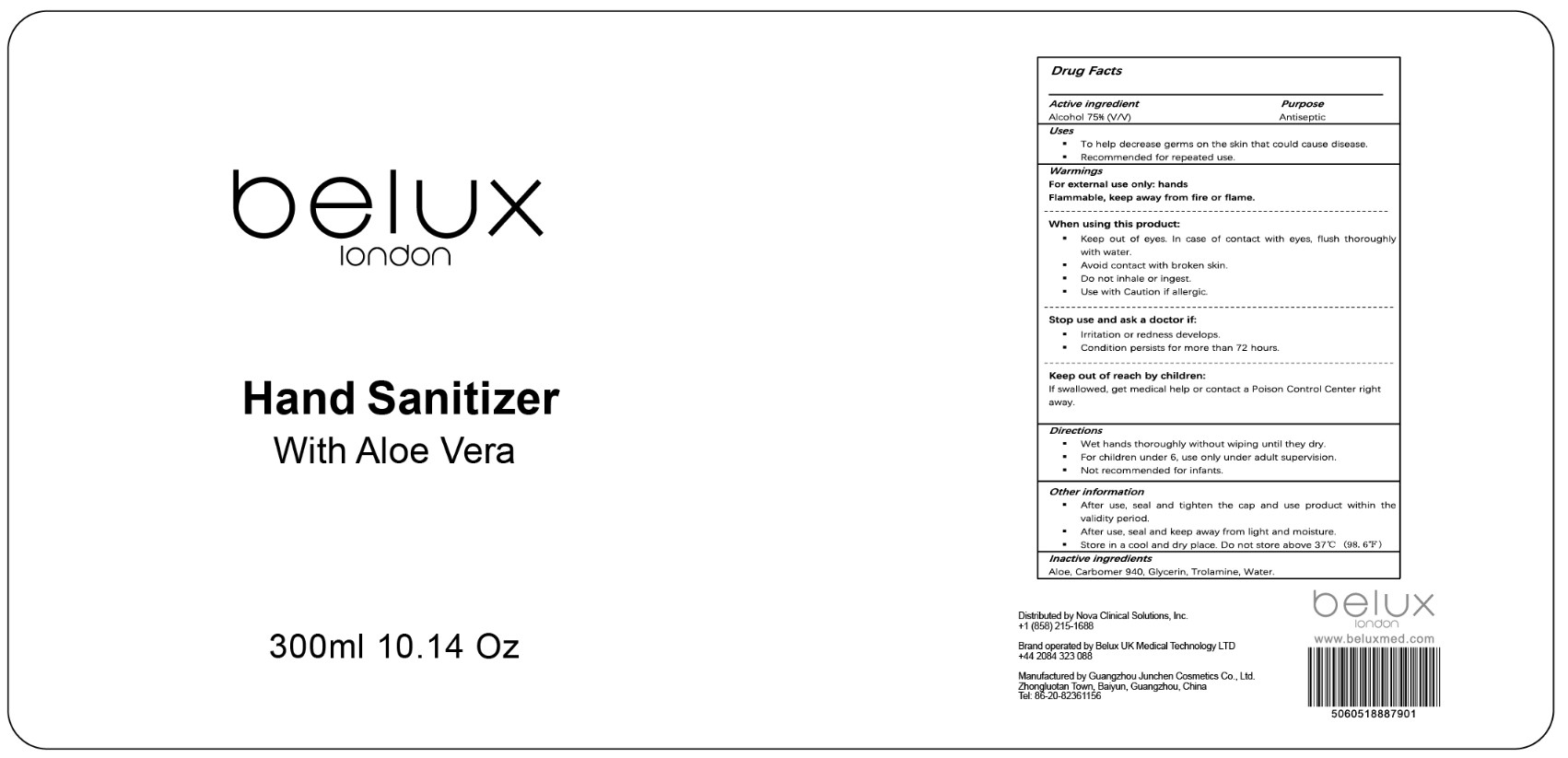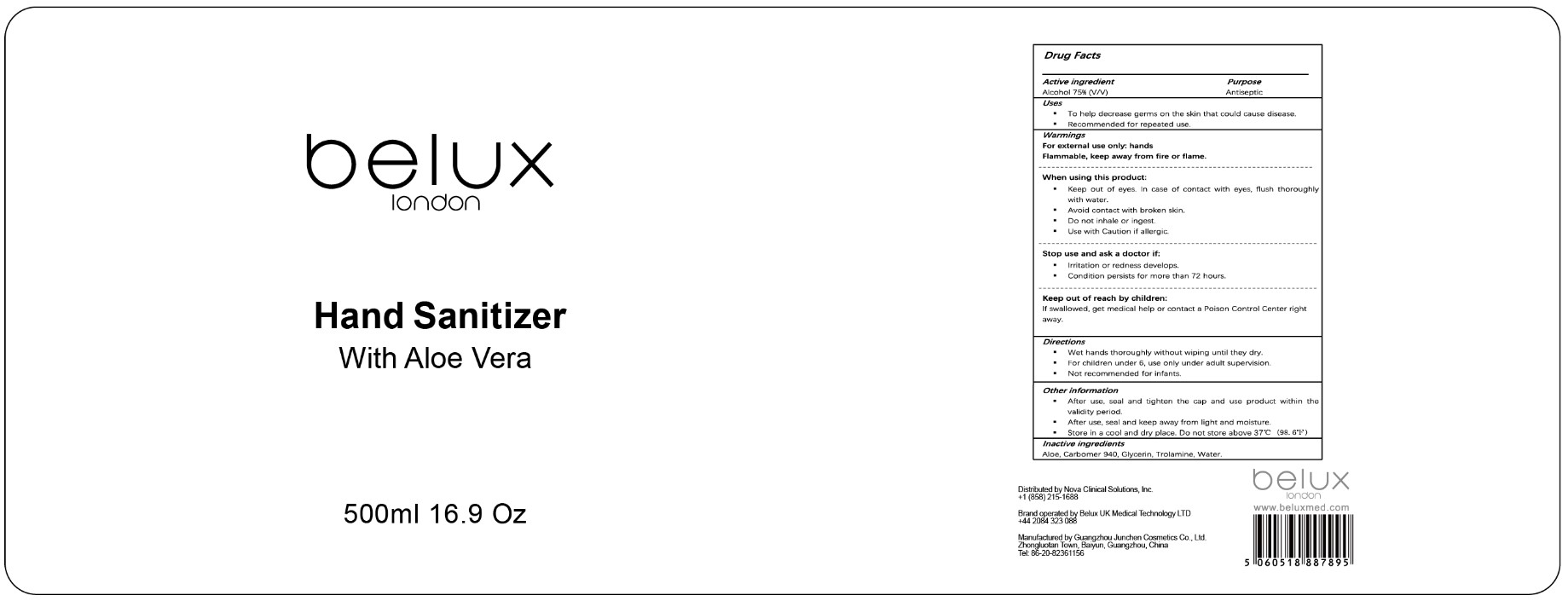 DRUG LABEL: Belux London Hand Sanitizer with Aloe Vera
NDC: 77084-001 | Form: GEL
Manufacturer: Belux UK Medical Technology Ltd
Category: otc | Type: HUMAN OTC DRUG LABEL
Date: 20200615

ACTIVE INGREDIENTS: ALCOHOL 75 mL/100 mL
INACTIVE INGREDIENTS: GLYCERIN 1.55 mL/100 mL; ALOE 0.05 mL/100 mL; WATER 19 mL/100 mL; CARBOMER 940 0.4 mL/100 mL; TROLAMINE 4 mL/100 mL

Active Ingredient

Alcohol 75% (v/v)

Purpose

Antiseptic

Uses

To help decrease germs on the skin that could cause disease.

Recommended for repeated use.

Warnings

For external use only: hands

Flammable, keep away from fire or flame.

When using this product:

Avoid contact with broken skin.
Do not inhale or ingest.
Use with Caution if allergic.

When using this product:

Keep out of eyes. In case of contact with eyes, flush thoroughly with water.
Avoid contact with broken skin.
Do not inhale or ingest.
Use with Caution if allergic.

Stop use and ask a doctor if:

Irritation or redness develops.
Condition persists for more than 72 hours.

Keep out of reach by children:

If swallowed, get medical help or contact a Poison Control Center right away.

Directions

Wet hands thoroughly without wiping until they dry.
For children under 6, use only under adult supervision.

Not recommended for infants.

Other information

After use, seal and tighten the cap and use product within the validity period.
After use, seal and keep away from light and moisture.

Store in a cool and dry place. Do not store above 37℃ (98.6℉)

Inactive ingredients

Aloe, Carbomer 940, Glycerin, Trolamine, Water.

Package Label - Principal Display Panel

100 mL NDC: 77084-001-01

300 mL NDC: 77084-001-02

500 mL NDC: 77084-001-03